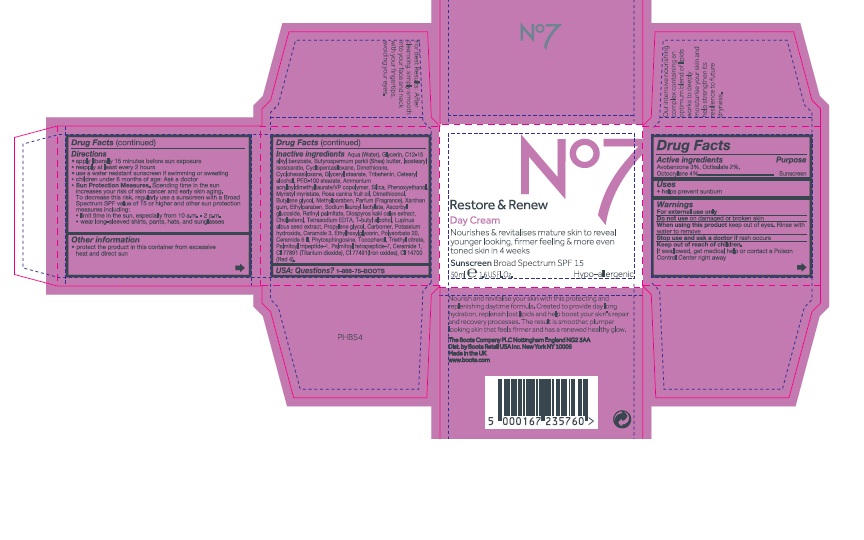 DRUG LABEL: No7 Restore and Renew Day Cream SPF 15
NDC: 11489-109 | Form: CREAM
Manufacturer: BCM Ltd
Category: otc | Type: HUMAN OTC DRUG LABEL
Date: 20161011

ACTIVE INGREDIENTS: AVOBENZONE 1.5 g/50 g; OCTOCRYLENE 2 g/50 g; OCTISALATE 1 g/50 g
INACTIVE INGREDIENTS: WATER; GLYCERIN; DIMETHICONE; ALKYL (C12-15) BENZOATE; ISOSTEARYL ISOSTEARATE; TRIBEHENIN; CYCLOMETHICONE 5; AMMONIUM ACRYLOYLDIMETHYLTAURATE/VP COPOLYMER; CYCLOMETHICONE 6; GLYCERYL STEARATE SE; PHENOXYETHANOL; CETOSTEARYL ALCOHOL; SHEA BUTTER; PEG-100 STEARATE; BUTYLENE GLYCOL; MYRISTYL MYRISTATE; ROSA CANINA FRUIT OIL; METHYLPARABEN; DIMETHICONOL (40 CST); ETHYLPARABEN; XANTHAN GUM; SODIUM LAUROYL LACTYLATE; VITAMIN A PALMITATE; ASCORBYL GLUCOSIDE; DIOSPYROS KAKI LEAF; EDETATE SODIUM; CHOLESTEROL; TERT-BUTYL ALCOHOL; LUPINUS ALBUS SEED OIL; PROPYLENE GLYCOL; POLYSORBATE 20; CARBOMER 940; POTASSIUM HYDROXIDE; ETHYLHEXYLGLYCERIN; CERAMIDE 3; CERAMIDE 6 II; TOCOPHEROL; PHYTOSPHINGOSINE; TITANIUM DIOXIDE; TRIETHYL CITRATE; PALMITOYL TETRAPEPTIDE-7; PALMITOYL TRIPEPTIDE-1; CERAMIDE 1; FD&C RED NO. 4

No7 Restore and Renew Day Cream Sunscreen Broad Spectrum SPF15

Carton Active Ingredients Section

Active ingredients

Avobenzone 3%

Octisalate 2%

Octocrylene 4%

Uses

Uses - helps prevent sunburn

Warnings

For external use only

Do not use on damaged or broken skin

When using this product keep out of eyes. Rinse with water to remove.

Ask a doctor

Stop use and ask a doctor if rash occurs

Keep out of reach of children

If swallowed, get medical help or contact a Poison Control Center right away

Directions

Apply liberally 15 minutes before sun exposure

reapply at least every 2 hours

use a water resistant sunscreen if swimming or sweating

children under 6 months of age: Ask a doctor

Sun Protection Measures. Spending time in the sun increases your risk of skin cancer and early skin aging.

To decrease this risk, regularly use a sunscreen with a Broad Spectrum SPF value of 15 or higher and other sun protection measures including:

Limit time in the sun, especially from 10 a.m - 2 p.m.

wear long-sleeved shirts,pants,hats and sunglasses.

Storage

Other information

Protect the product in this container from excessive heat and direct sun

Avoid contact with fabrics

Inactive ingredients

Aqua(Water), Glycerin, C12-15 alkyl bezoate, Butyrospermum parkii (Shea) butter, Isostearyl isostearate, Cyclopentasiloxane, Dimethicone, Cyclohexasiloxane, Glyeryl stearate, Tribehenin, Cetearyl alcohol, PEG-100 stearate, Ammonium acryloyldimethyltaurate/VP copolymer, Silica, Phenoxyethanol, Myristyl myristate, Rosa canina fruit oil, Dimethiconol, Butylene glycol, Methylparaben, Parfum(Fragrance), Xanthan gum, Ethylparaben, Sodium lauroyl lactylate, Ascorbyl glucoside, Retinyl palmitate, Diospyros kaki calyx extract, Cholesterol, Tetrasodium EDTA, T-butyl alcohol, Lupinus albus seed extract, Propylene glycol, Carbomer, Potassium hydroxide, Ceramide 3, Ethylhexylglycerin, Polysorbate 20, Ceramide 6 ll, Phytosphingosine, Tocopherol, Triethyl citrate, Palmitoyl tripeptide-1, Palmitoyl tetrapeptide-7, Ceramide 1, CI77891(Titanium dioxide) CI 77491(Iron oxides), CI14700(Red 4)

PATIENT COUNSELING INFORMATION

The Boots Company PLC Nottingham England NG2 3AA

Dist. by Boots Retail USA Inc. New York NY 10005

Made in the UK

www.boots.com

Description

Nourishes and revitalises maure skin to reveal younger looking, firmer feeling and more even toned skin in 4 weeks.

Nourish and revitalise your skin with this protecting and replenishing daytime formula. Created to provide day long hydration, replenish lost lipids and help boost your skin's repair and recovery processes. The result is smoother,plumper looking skin that feels fimer and has a renewed healthy glow.

Our intensive nourishing complex containing an optimum blend of lipids works to deeply moisturise your skin and help strengthen its resilience to future dryness.

For Best Results: